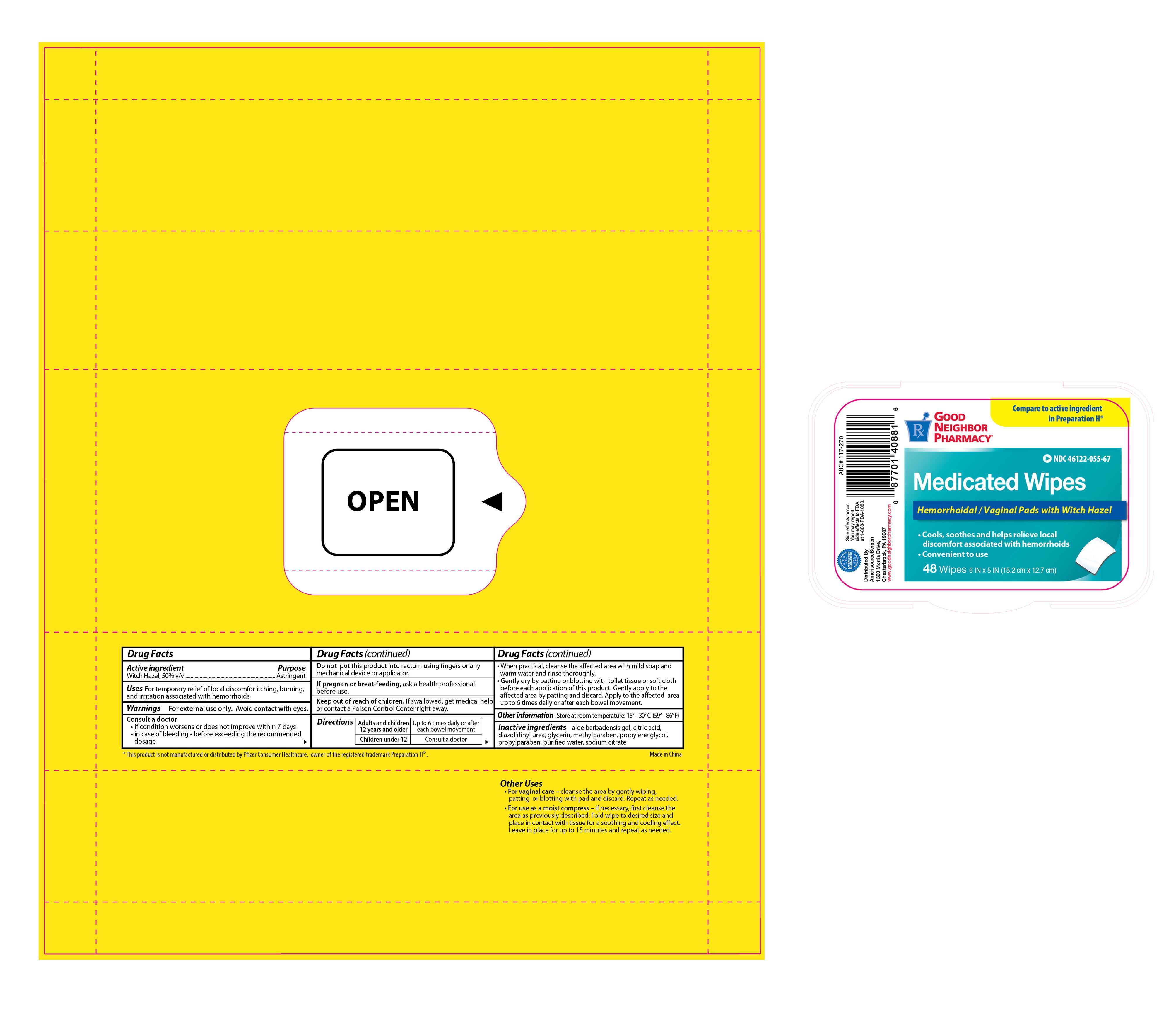 DRUG LABEL: GNP Medicated Wipes
NDC: 46122-055 | Form: SOLUTION
Manufacturer: Amerisource Bergen
Category: otc | Type: HUMAN OTC DRUG LABEL
Date: 20130630

ACTIVE INGREDIENTS: WITCH HAZEL 0.5 mg/1 mg
INACTIVE INGREDIENTS: CITRIC ACID MONOHYDRATE; DIAZOLIDINYL UREA; GLYCERIN; METHYLPARABEN; PROPYLENE GLYCOL; PROPYLPARABEN; WATER; SODIUM CITRATE

Drug Facts

Active ingredient Purpose

Witch Hazel, 50% v/v...................................................Astringent

PURPOSE

Uses For temporary relief of local discomfort itching, burning, and irritation associated with hemorrhoids

WARNINGS

Warnings For external use only. Avoid contact with eyes.

Consult a doctor

- if condition worsens or does not improve within 7 days
- in case of bleeding
- before exceeding the recommended dosage

DO NOT USE

Do not put this product into rectum using fingers or any mechanical device or applicator.

PREGNANCY OR BREAST FEEDING

If pregnant or breast-feeding, ask a health professional before use.

Keep out of reach of children. If swallowed, get medical help or contact a Poison Control Center right away.

Directions

- Adults and children 12 years and older: up to 6 times daily or after each bowel movement
- Children under 12: consult a doctor
- When practical, cleanse the affected area with mild soap and warm water and rinse thoroughly
- Gently dry by patting or blotting with toilet tissue or soft cloth before each application of this product. Gently apply to the affected area by patting and discard. Apply to the affected area up to 6 times daily or after each bowel movement.

Other information Store at room temperature: 15° - 30 °C (59° - 86°F)

Inactive ingredient aloe barbadensis gel, citric acid, diazolidinyl urea, glycerin, methylparaben, propylene glycol, propylparaben, purified water, sodium citrate

DOSAGE AND ADMINISTRATION

Distributed By

Amerisource Bergen

1300 Morris Drive

Chesterbrook, PA 19067